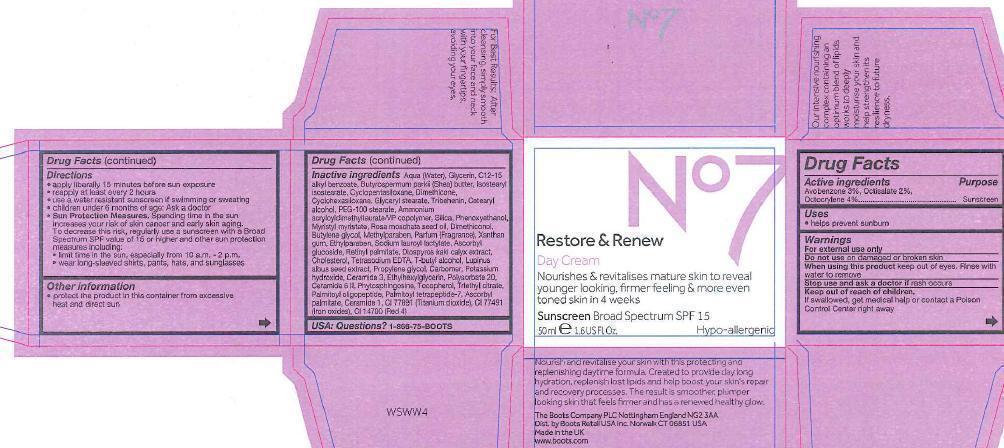 DRUG LABEL: No7 Restore and Renew Day Sunscreen
NDC: 11489-078 | Form: CREAM
Manufacturer: BCM Ltd
Category: otc | Type: HUMAN OTC DRUG LABEL
Date: 20121210

ACTIVE INGREDIENTS: AVOBENZONE 1.5 g/50 g; OCTISALATE 1 g/50 g; OCTOCRYLENE 2 g/50 g
INACTIVE INGREDIENTS: WATER; GLYCERIN; C12-15 ALKYL BENZOATE; SHEA BUTTER; ISOSTEARYL ISOSTEARATE; CYCLOMETHICONE 5; DIMETHICONE; CYCLOMETHICONE 6; GLYCERYL STEARATE SE; TRIBEHENIN; CETOSTEARYL ALCOHOL; PEG-100 STEARATE; AMMONIUM ACRYLOYLDIMETHYLTAURATE/VP COPOLYMER; PHENOXYETHANOL; MYRISTYL MYRISTATE; ROSA MOSCHATA SEED OIL; BUTYLENE GLYCOL; METHYLPARABEN; XANTHAN GUM; ETHYLPARABEN; SODIUM LAUROYL LACTYLATE; ASCORBYL GLUCOSIDE; VITAMIN A PALMITATE; CHOLESTEROL; EDETATE SODIUM; PROPYLENE GLYCOL; POTASSIUM HYDROXIDE; CERAMIDE 3; ETHYLHEXYLGLYCERIN; POLYSORBATE 20; CERAMIDE 6 II; PHYTOSPHINGOSINE; TOCOPHEROL; TRIETHYL CITRATE; PALMITOYL OLIGOPEPTIDE; PALMITOYL TETRAPEPTIDE-7; ASCORBYL PALMITATE; CERAMIDE 1; TITANIUM DIOXIDE

No7 Restore and Renew Day Cream

Warnings

For external use only

Do not use on damaged or broken skin

When using this product keep out of eyes. Rinse with water to remove

Ask a doctor

Stop use and ask a doctor if rash occurs

Keep out of reach of children. If swallowed, get medical help or contact a Poison Center right away

Directions

Directions for sunscreen use

apply liberally 15 minutes before sun exposure

reapply at least every 2 hours

use a water resistant sunscreen if swimming or sweating

children under 6 months of age: Ask a doctor

Sun Protection Measures. Spending time in the sun increases your risk of skin cancer and eraly skin aging. Todecrease this risk, regularly use a sunscreen with a Broad spectrum SPF value of 15 or higher and other sun protection measures including:

limit time in the sun,especially from 10 a.m. - 2 p.m.

wear long-sleeved shirts, pants,hates, and sunglasses

Storage

Other information - protect the product in this container from excessive heat and direct sun

Inactive ingredients

Aqua (Water), Glycerin, C12-15 alkyl benzoate,Butrospermum parkii (Shea) butter, Isostearyl isostearate, Cyclopentasiloxane, Dimethicone, Cyclohexasiloxane, Glyceryl stearate, Tribehenin, Cetearyl alcohol, PEG-100 stearate, Ammonium acryloydimethyltaurate/VP copolymer, Silica, Phenoxyethanol,Myristyl myristate, Rosa moschata seed oil, Dimethiconol, Butylene glycol, Methylparaben, Parfum (Fragrance), Xanthan gum, Ethylparaben, Sodium lauroyl lactylate, Ascorbyl glucoside, Retinyl palmitate, Diospyros kaki calyx extract, Cholesterol, Tetrasodium EDTA, T-butyl-alcohol, Lupinus seed extract, Propylene glycol, carbomer, Potassium hydroxide, Ceramide 3, Ethylhexylglycerin, Polysorbate 20, Ceramide 6 II, Phytosphingosine, Tocopherol, Triethyl citrate, Palmitoyl oligopeptide, Palmitoyl tetrapeptide-7,Ascorbyl palmitate, Ceramide 1, CI 77891 (Titanium dioxide),CI 77491 (iron oxides), CI 14700 (Red4)

Description

Nourish and revitalise your skin with this protecting and replenishing daytime formula. Created to provide day long hydration, replenish lost lipids and help boost your skin's repair and recovery processes.The result is smoother, plumper looking skin that feels firmer and has a renewed healthy glow. Our inensive noursihing complex containing an optimum blend of lipids works to deeply moisturise your skin and help strengthen its resilience to future dryness.

For Best Results: After claensing, simply smooth into your face and neck with your fingertips, avoiding your eyes.

Information

The Boots Company PLC Nottingham England NG2 3AA

Dist. by Boots Retail USA Inc, Norwalk CT 06851 USA

Made in the UK

www.boots.com

Carton Active Ingredients Section

Active Ingredients

Avobenzone 3%

Octisalate 2%

Octocrylene 4%

Purpose Sunscreen

Uses

Uses - helps prevent sunburn

Printed jar

No7 Restore and Renew Day Cream Sunscreen Broad Spectrum SPF 15

50ml e 1.6 US Fl.Oz.

Active ingredients: Avobenzone 3%, Octisalate 2%, Octocrylene 4%

Warning

Avoid contact with eyes. If product gets into the eyes rinse well with water immediately.

Description

smooth into your face and neck after applying your No7 serum

Information

The Boots Company PLC

Nottingham England NG2 3AA

Dist by Boots Retail USA Inc.

Norwalk CT 06851 USA

Made in the UK

www.boots.com

carton